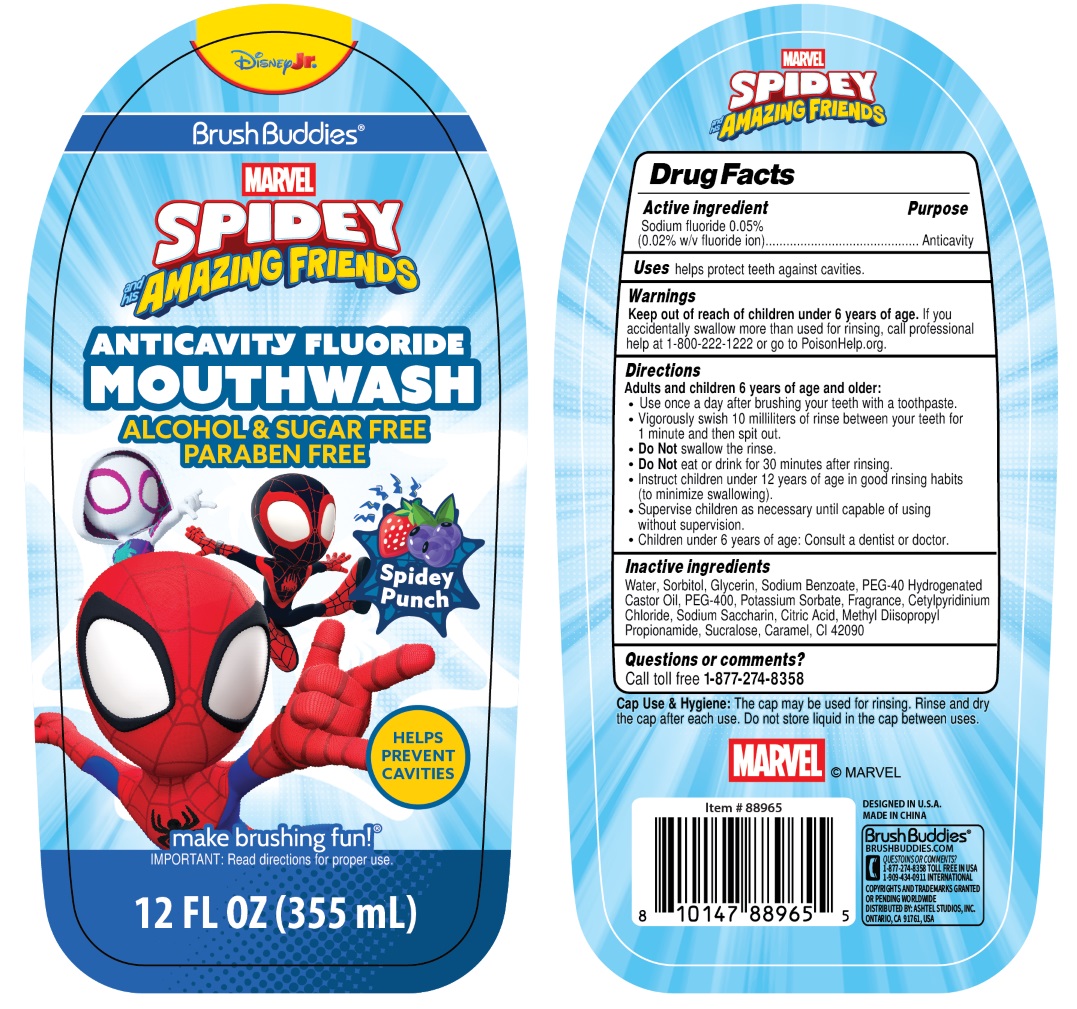 DRUG LABEL: Brush Buddies SPIDEY and his AMAZING FRIENDS ANTICAVITY FLUORIDE-Spidey Punch
NDC: 70108-316 | Form: MOUTHWASH
Manufacturer: Ashtel Studios Inc.
Category: otc | Type: HUMAN OTC DRUG LABEL
Date: 20260128

ACTIVE INGREDIENTS: SODIUM FLUORIDE 0.05 g/100 mL
INACTIVE INGREDIENTS: WATER; SORBITOL; GLYCERIN; SODIUM BENZOATE; POLYOXYL 40 HYDROGENATED CASTOR OIL; POLYETHYLENE GLYCOL 400; POTASSIUM SORBATE; CETYLPYRIDINIUM CHLORIDE; SACCHARIN SODIUM; CITRIC ACID MONOHYDRATE; METHYL DIISOPROPYL PROPIONAMIDE; SUCRALOSE; CARAMEL; FD&C BLUE NO. 1

Brush Buddies® SPIDEY and his AMAZING FRIENDS ANTICAVITY FLUORIDE MOUTHWASH-Spidey Punch

Active ingredient

Sodium fluoride 0.05%
(0.02% w/v fluoride ion)

Purpose

Anticavity

Uses

helps protect teeth against cavities.

Warnings

Keep out of reach of children under 6 years of age. If you accidentally swallow more than used for rinsing, call professional help at 1-800-222-1222 or go to PoisonHelp.org.

Directions

Adults and children 6 years of age and older:
• Use once a day after brushing your teeth with a toothpaste.
• Vigorously swish 10 milliliters of rinse between your teeth for 1 minute and then spit out.
• Do Not swallow the rinse.
• Do Not eat or drink for 30 minutes after rinsing.
• Instruct children under 12 years of age in good rinsing habits (to minimize swallowing).
• Supervise children as necessary until capable of using without supervision.
• Children under 6 years of age: Consult a dentist or doctor.

Inactive ingredients

Water, Sorbitol, Glycerin, Sodium Benzoate, PEG-40 Hydrogenated Castor Oil, PEG-400, Potassium Sorbate, Fragrance, Cetylpyridinium Chloride, Sodium Saccharin, Citric Acid, Methyl Diisopropyl Propionamide, Sucralose, Caramel, CI 42090

Questions or comments?

Call toll free 1-877-274-8358

DISNEYJr.

MARVEL

ALCOHOL & SUGAR FREE
PARABEN FREE

HELPS PREVENT CAVITIES

make brushing fun!®
IMPORTANT: Read directions for proper use.

Cap Use & Hygiene: The cap may be used for rinsing. Rinse and dry cap after each use. Do not store liquid in cap between uses.

DESIGNED IN U.S.A.
MADE IN CHINA

BRUSHBUDDIES.COM

COPYRIGHTS AND TRADEMARKS GRANTED OR PENDING WORLDWIDE
DISTRIBUTED BY: ASHTEL STUDIOS, INC.
ONTARIO, CA 91761, USA